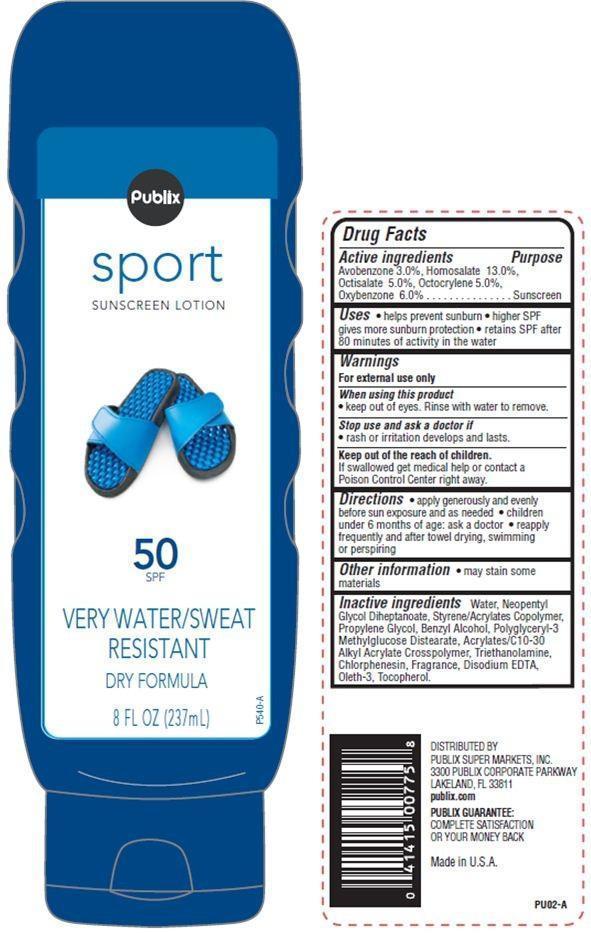 DRUG LABEL: Publix Sport
NDC: 56062-707 | Form: LOTION
Manufacturer: Publix Super Markets Inc
Category: otc | Type: HUMAN OTC DRUG LABEL
Date: 20121114

ACTIVE INGREDIENTS: AVOBENZONE 3 g/100 g; HOMOSALATE 13 g/100 g; OCTISALATE 5 g/100 g; OCTOCRYLENE 5 g/100 g; OXYBENZONE 6 g/100 g
INACTIVE INGREDIENTS: WATER; PROPYLENE GLYCOL; BENZYL ALCOHOL; TROLAMINE; CHLORPHENESIN; EDETATE DISODIUM; TOCOPHEROL

Drug Facts

Active ingredients

Avobenzone 3.0%
Homosalate 13.0%
Octisalate 5.0%
Octocrylene 5.0%
Oxybenzone 6.0%

Purpose

Sunscreen

Uses

- helps prevent sunburn
- higher SPF gives more sunburn protection
- retains SPF after 80 minutes of activity in water

Warnings

For external use only

When using this product

- keep out of eyes. Rinse with water to remove.

Stop use and ask a doctor if

- rash or irritation develops or lasts.

Keep out of the reach of children.
If swallowed get medical help or contact a Poison Control Center right away.

Directions

- apply generously and evenly before sun exposure and as needed
- children under 6 months of age: ask a doctor
- reapply frequently and after towel drying, swimming or perspiring

Other information

- may stain some materials

Inactive ingredients

Water, Neopentyl Glycol Diheptanoate, Styrene/Acrylates Copolymer, Propylene Glycol, Polyglyceryl-3 Methylglucose Distearate, Benzyl Alcohol, Acrylates/C10-30 Alkyl Acrylate Crosspolymer, Triethanolamine, Disodium EDTA, Oleth-3, Tocopherol, Chlorphenesin, Fragrance.

Principal Display Panel

Publix
sport sunscreen lotion
50 SPF
VERY WATER/SWEAT RESISTANT
DRY FORMULA
8 FL OZ(237 mL)